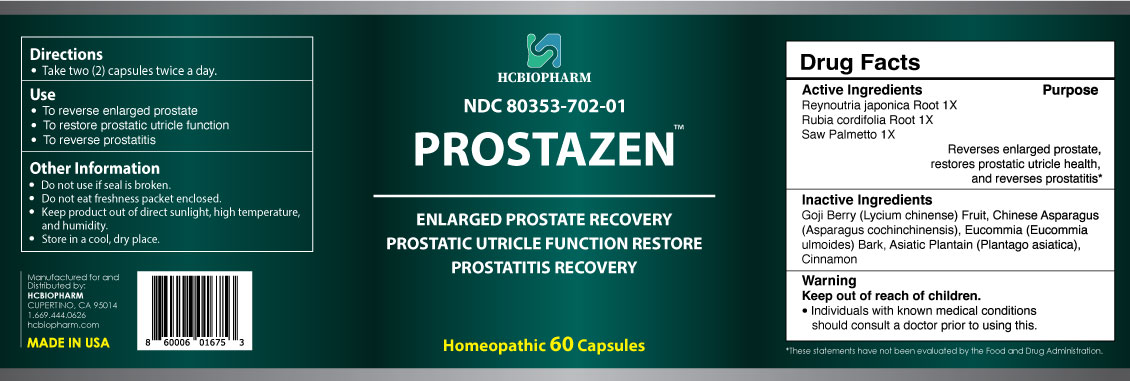 DRUG LABEL: Prostazen
NDC: 80353-702 | Form: CAPSULE
Manufacturer: HCBIOPHARM LLC
Category: homeopathic | Type: HUMAN OTC DRUG LABEL
Date: 20250103

ACTIVE INGREDIENTS: SAW PALMETTO 1 [hp_X]/1 1; RUBIA CORDIFOLIA ROOT 1 [hp_X]/1 1; REYNOUTRIA JAPONICA ROOT 1 [hp_X]/1 1
INACTIVE INGREDIENTS: LYCIUM CHINENSE FRUIT; PLANTAGO ASIATICA; ASPARAGUS COCHINCHINENSIS WHOLE; EUCOMMIA ULMOIDES BARK; CINNAMON

Active Ingredients

Reynoutria japonica Root 1X, Rubia cordifolia Root 1X, Saw Palmetto 1X

Purpose

Reverses enlarged prostate, restores prostatic utricle function, and reverses prostatitis*

Keep Out of Reach of Children

Directions

Take two (2) capsules twice a day.

Use

- To reverse enlarged prostate
- To restore prostatic utricle function
- To reverse prostatitis

Inactive Ingredients

Goji Berry (Lycium chinense) Fruit, Chinese Asparagus (Asparagus cochinchinensis), Eucommia (Eucommia ulmoides) Bark, Asiatic Plantain (Plantago asiatica), Cinnamon

Warning

Individuals with known medical conditions should consult a doctor prior to using this.

Other Information

- Do not use if seal is broken.
- Do not eat freshness packet enclosed.
- Keep product out of direct sunlight, high temperature, and humidity.
- Store in a cool, dry place.

Package Label Display

Prostazen™

ENLARGED PROSTATE RECOVERY
PROSTATIC UTRICLE FUNCTION RESTORE
PROSTATITIS RECOVERY

Homeopathic 60 Capsules